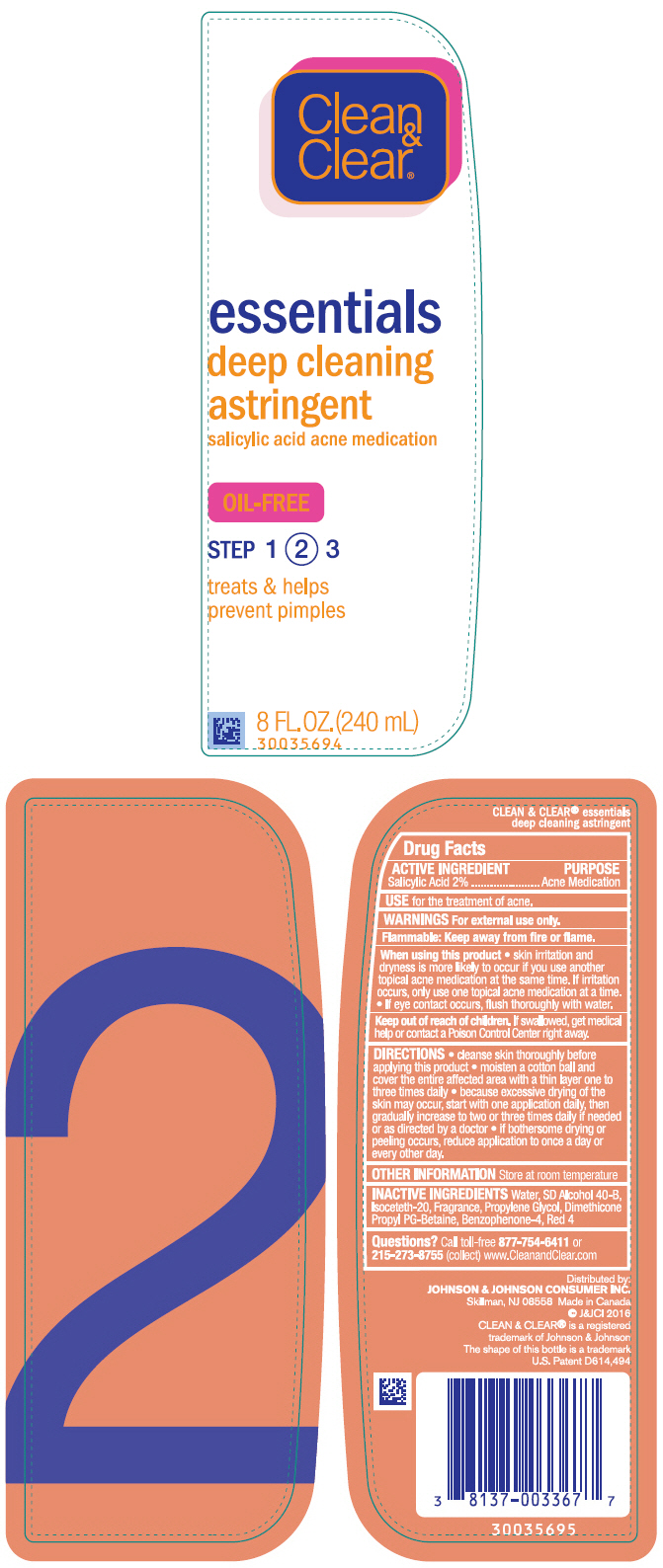 DRUG LABEL: Clean and Clear Essentials Deep Cleaning
NDC: 69968-0209 | Form: LIQUID
Manufacturer: Kenvue Brands LLC
Category: otc | Type: HUMAN OTC DRUG LABEL
Date: 20241106

ACTIVE INGREDIENTS: SALICYLIC ACID 20 mg/1 mL
INACTIVE INGREDIENTS: DIMETHICONE PROPYL PG-BETAINE; WATER; ALCOHOL; ISOCETETH-20; SULISOBENZONE; FD&C RED NO. 4; PROPYLENE GLYCOL

Clean & Clear® essentials deep cleaning astringent

Drug Facts

ACTIVE INGREDIENT

Salicylic Acid 2%

PURPOSE

Acne Medication

USE

for the treatment of acne.

WARNINGS

For external use only.

Flammable: Keep away from fire or flame.

When using this product

- skin irritation and dryness is more likely to occur if you use another topical acne medication at the same time. If irritation occurs, only use one topical acne medication at a time.
- If eye contact occurs, flush thoroughly with water.

Keep out of reach of children. If swallowed, get medical help or contact a Poison Control Center right away.

DIRECTIONS

- cleanse skin thoroughly before applying this product
- moisten a cotton ball and cover the entire effected area with a thin layer one to three times daily
- because excessive drying of the skin may occur, start with one application daily, then gradually increase to two or three times daily if needed or as directed by a doctor
- if bothersome drying or peeling occurs, reduce application to once a day or every other day.

OTHER INFORMATION

Store at room temperature

INACTIVE INGREDIENTS

Water, SD Alcohol 40-B, Isoceteth-20, Fragrance, Propylene Glycol, Dimethicone Propyl PG-Betaine, Benzophenone-4, Red 4

Questions?

Call toll-free 877-754-6411 or 215-273-8755 (collect) www.CleanandClear.com

Distributed by:
JOHNSON & JOHNSON CONSUMER INC.
Skillman, NJ 08558

PRINCIPAL DISPLAY PANEL - 240 mL Bottle Label

Clean
&
Clear®

essentials
deep cleaning
astringent
salicylic acid acne medication

OIL-FREE

STEP 1 (2) 3

treats & helps
prevent pimples

8 FL. OZ. (240mL)